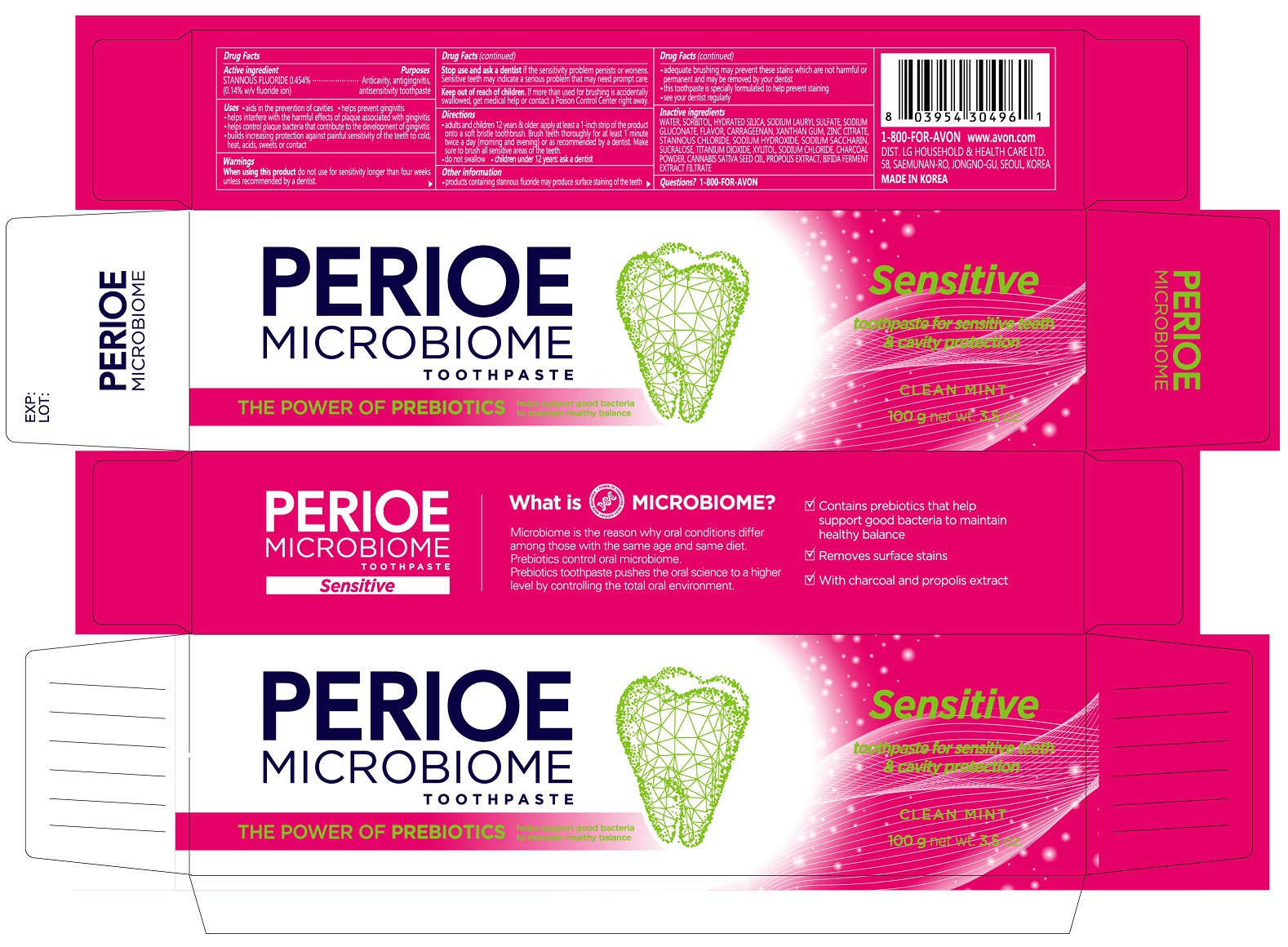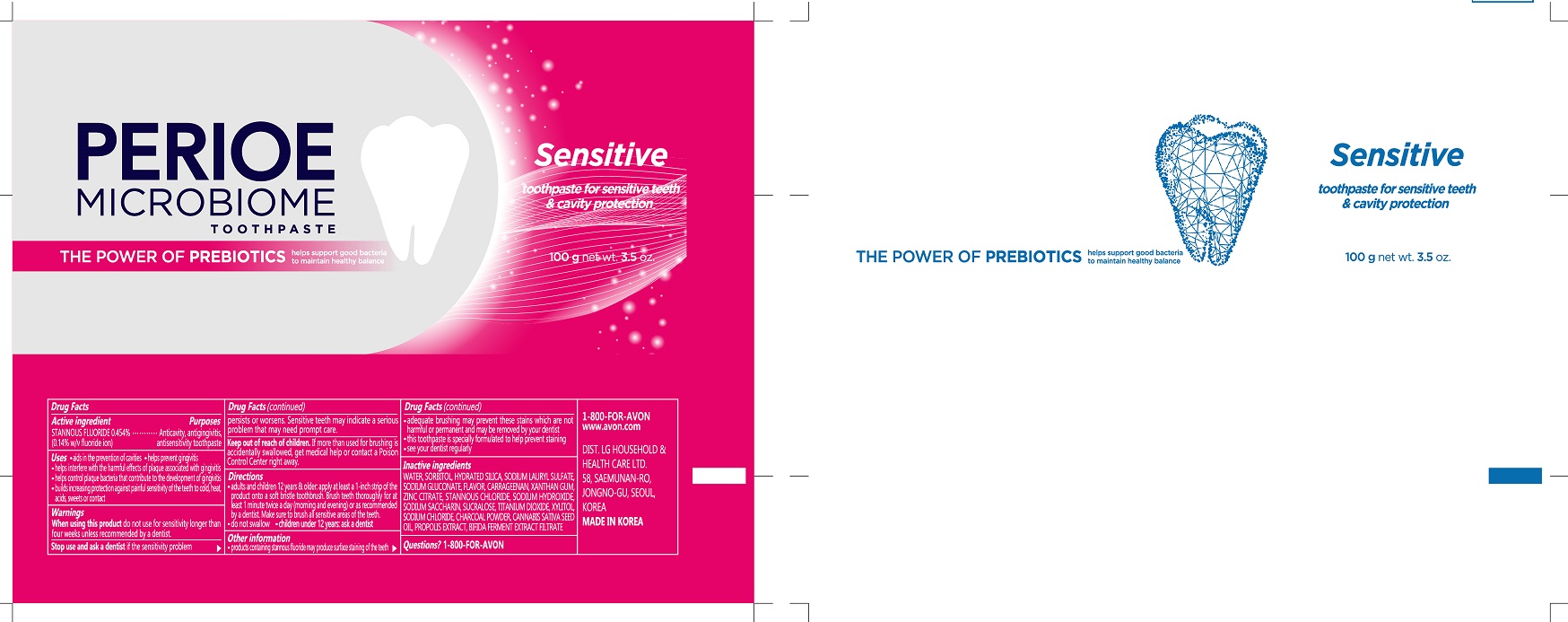 DRUG LABEL: PERIOE Microbiome Sensitive
NDC: 43136-830 | Form: PASTE, DENTIFRICE
Manufacturer: Tai Guk Pharm. Co., Ltd.
Category: otc | Type: HUMAN OTC DRUG LABEL
Date: 20250101

ACTIVE INGREDIENTS: STANNOUS FLUORIDE 1.4 mg/1 g
INACTIVE INGREDIENTS: SUCRALOSE; HYDRATED SILICA; PROPOLIS WAX; SORBITOL; WATER; SODIUM GLUCONATE; CARRAGEENAN; SODIUM LAURYL SULFATE; XYLITOL; SACCHARIN SODIUM; STANNOUS CHLORIDE; TITANIUM DIOXIDE; ZINC CITRATE; SODIUM CHLORIDE; SODIUM HYDROXIDE; XANTHAN GUM; ACTIVATED CHARCOAL; CANNABIS SATIVA SEED OIL

PERIOE Microbiome Sensitive Toothpaste Clean Mint 100 g

Drug Facts

Active Ingredient

STANNOUS FLUORIDE 0.454% (0.14% w/v fluoride ion)

Purposes

Anticavity, antigingivitis, antisensitivity toothpaste

Uses

- aids in the prevention of cavities
- helps prevent gingivitis
- helps interfere with the harmful effects of plaque associated with gingivitis
- helps control plaque bacteria that contribute to the develpment of gingivitis
- builds increasing protection against painful sensitivity of the teeth to cold, heat, acids, sweets or contact

Warnings

When using this product

When using this productdo not use for sensitivity longer than four weeks unless recommended by a dentist.

Stop use and ask a dentist

Stop use and ask a dentistif the sensitivity problem persits or worsens. Sensitive teeth may indicate a serious problem that may need prompt care.

Keep out of reach of children.If more than used for brushing is accidentally swallowed, get medical help or contact a Poison Control Center right away.

Directions

- adults and children 12 years & older: apply at least a 1-inch strip of the product onto a soft bristle toothbrush. Brush teeth thoroughly for at least 1 minute twice a day (morning and evening) or as recommended by a dentist. Make sure to brush all sensitive areas of the teeth.
- do not swallow
- children under 12 years: ask a dentist.

Other information

- products containing stannous fluoride may produce surface staining of the teeth
- adequate brushing may prevent these stains which are not harmful or permanent and may be removed by your dentist
- this toothpaste is specially formulated to help prevent staining
- see your dentist regularly

Inactive Ingredients

WATER, SORBITOL, HYDRATED SILICA, SODIUM LAURYL SULFATE, SODIUM GLUCONATE, FLAVOR, CARRAGEENAN, XANTHAN GUM, ZINC CITRATE, STANNOUS CHLORIDE, SODIUM HYDROXIDE, SODIUM SACCHARIN, SUCRALOSE, TITANIUM DIOXIDE, XYLITOL, SODIUM CHLORIDE, CHARCOAL POWDER, CANNABIS SATINA SEED OIL, PROPOLIS EXTRACT, BIFIDA FERMENT EXTRACT FILTRATE

Questions?

1-800-FOR-AVON

Principal Display Panel - 100 g Tube Carton

PERIOE
MICROBIOME
TOOTHPASTE

THE POWER OF PREBIOTICS
helps support good bacteria
to maintain healthy balance

Sensitive

toothepaste for sensitive teeth
& cavity protection
CLEAN MINT

100 g net wt. 3.5 oz